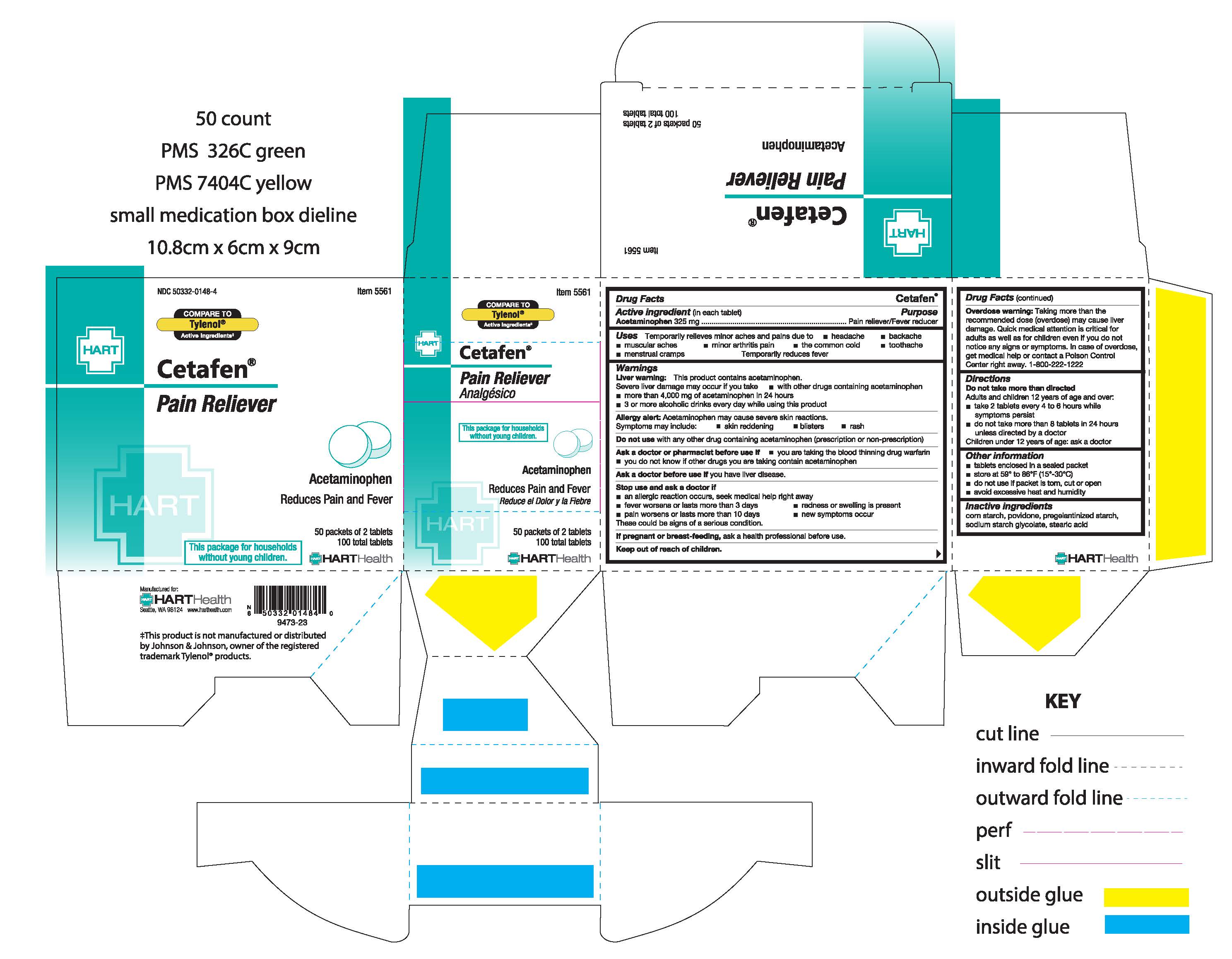 DRUG LABEL: CETAFEN
NDC: 50332-0148 | Form: TABLET
Manufacturer: HART Health
Category: otc | Type: HUMAN OTC DRUG LABEL
Date: 20251224

ACTIVE INGREDIENTS: ACETAMINOPHEN 325 mg/1 1
INACTIVE INGREDIENTS: STARCH, CORN; POVIDONE; SODIUM STARCH GLYCOLATE TYPE A CORN; STEARIC ACID

CETAFEN

Active Ingredient (in each tablet): Acetaminophen 325mg

Purpose:

Pain Reliever/Fever Reducer

Uses:

Temporarily relieves minor aches and pains due to:

- headache
- muscular aches
- backache
- minor arthritis pain
- the common cold
- toothache
- menstrual cramps

Temporarily reduces fever

Warnings:

Liver warning: This product contains acetaminophen. Severe liver damage may occur if you take:

- more than 4,000 mg of acetaminophen in 24 hours
- with other drugs containing acetaminophen
- 3 or more alcoholic drinks every day while using this product

Allergy alert: Acetaminophen may cause severe skin reactions. Symptoms may include:

- skin reddening
- rash
- blisters

Do not use with any other drug containing acetaminophen (prescription or non-prescription)

Ask a doctor or pharmacist before use if:

- you are taking the blood thinning drug warfarin
- you do not know if other drugs you are taking contain acetaminophen

Ask a doctor before use if you have liver disease

Stop use and ask a doctor if:

- an allergic reaction occurs, seek medical help right away
- new symptoms occur
- redness or swelling is present
- fever worsens or lasts for more than 3 days
- pain worsens or lasts for more than 10 days

These could be signs of a serious condition

PREGNANCY OR BREAST FEEDING

If pregnant or breast-feeding, ask a health professional before use

Keep out of reach of children

OVERDOSAGE

Overdose warning: Taking more than the recommended dose (overdose) may cause liver damage. Quick medical attention is critical for adults as well as for children even if you do not notice any signs or symptoms. In case of overdose, get medical help or contact Poison Control Center right away. 1-800-222-1222

Directions:

Do not take more than directed.

Adults and children 12 year of age and over:

- take 2 tables every 4 to 6 hours while symptoms persist
- do not take more than 8 tablets in 24 hours unless directed by a doctor

Children under 12 years of age: ask a doctor

Other information:

- tablets enclosed in a sealed packet
- do not use if packet is torn, cut or open
- store at 59° to 86°F (15°-30°C)
- avoid excessive heat and humidity

INACTIVE INGREDIENT

Inactive Ingredients: corn Starch, povidone, pregelantized starch, sodium starch glycolate, stearic acid